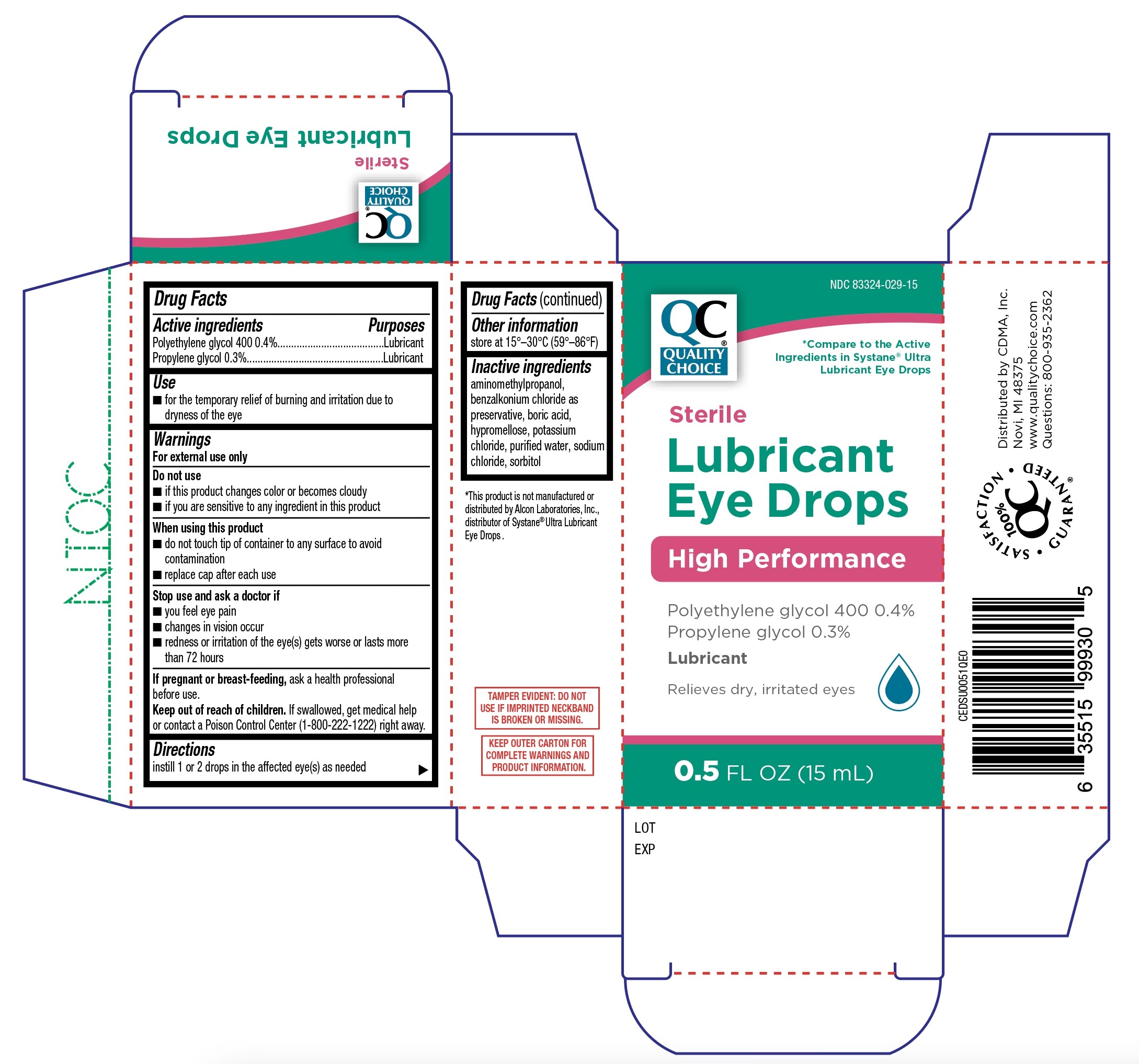 DRUG LABEL: Quality Choice Lubricant Eye Drops High Performance
NDC: 83324-029 | Form: SOLUTION/ DROPS
Manufacturer: Chain Drug Marketing Assoc., Inc.
Category: otc | Type: HUMAN OTC DRUG LABEL
Date: 20251230

ACTIVE INGREDIENTS: POLYETHYLENE GLYCOL 400 0.4 g/100 mL; PROPYLENE GLYCOL 0.3 g/100 mL
INACTIVE INGREDIENTS: SORBITOL; WATER; BENZALKONIUM CHLORIDE; HYPROMELLOSE, UNSPECIFIED; POTASSIUM CHLORIDE; SODIUM CHLORIDE; AMINOMETHYLPROPANOL; BORIC ACID

Quality Choice Lubricant Eye Drops High Performance 15mL (PLD)

Active ingredients

Polyethylene glycol 400 0.4%

Propylene glycol 0.3%

Purposes

Lubricant

Lubricant

Use

- for the temporary relief of burning and irritation due to dryness of the eye

Warnings

For external use only

Do not use

- if this product changes color or becomes cloudy
- if you are sensitive to any ingredient in this product

When using this product

- do not touch tip of container to any surface to avoid contamination
- replace cap after each use

Stop use and ask a doctor if

- you feel eye pain
- changes in vision occur
- redness or irritation of the eye(s) gets worse or lasts more than 72 hours

If pregnant or breast-feeding,

ask a health professional before use.

Keep out of reach of children.

If swallowed, get medical help or contact a Poison Control Center (1-800-222-1222) right away.

Directions

instill 1 or 2 drops in the affected eye(s) as needed

Other information

store at 15º-30ºC (59º-86ºF)

Inactive ingredients

aminomethylpropanol, benzalkonium chloride as preservative, boric acid, hypromellose, potassium chloride, purified water, sodium chloride, sorbitol;